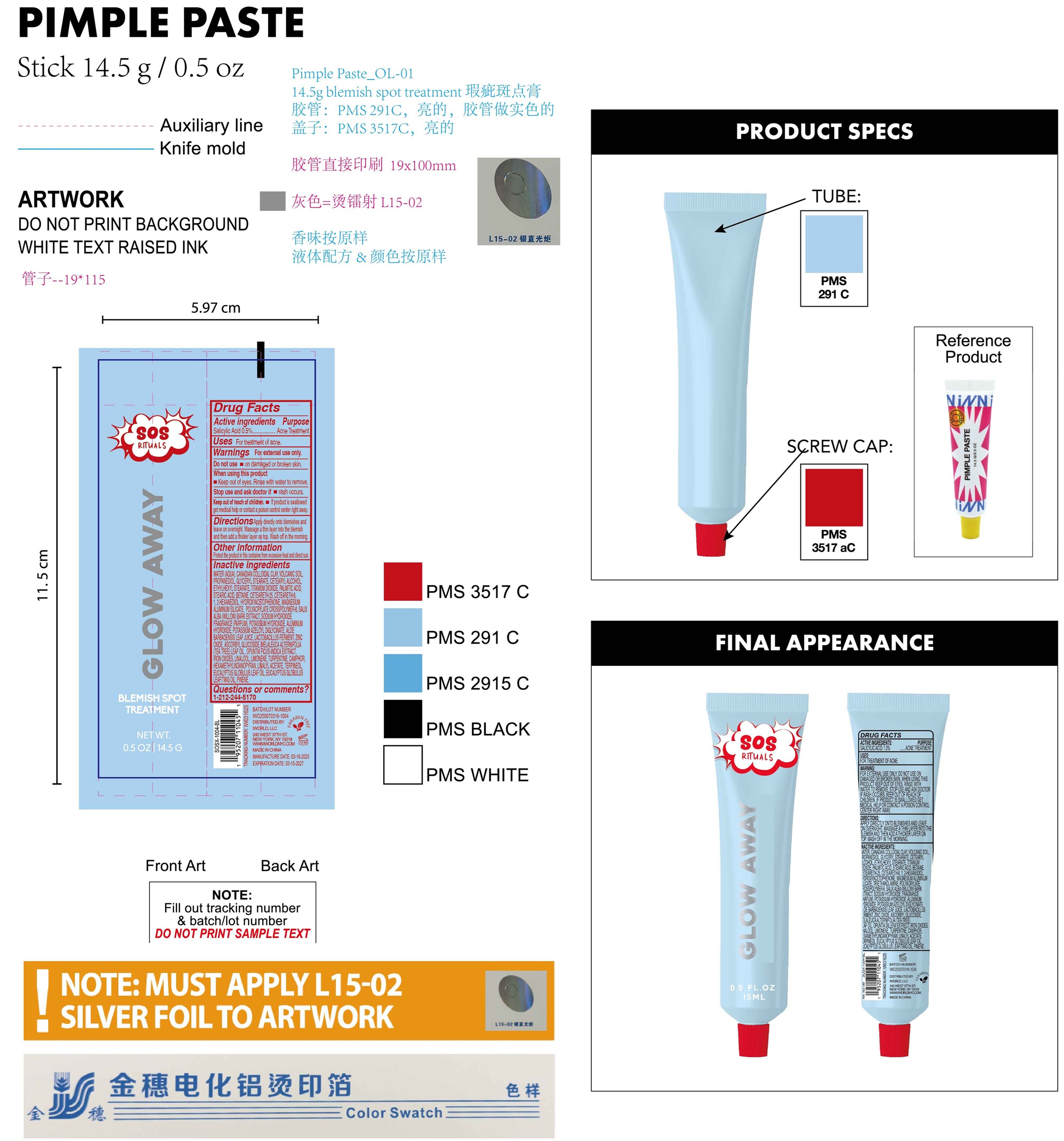 DRUG LABEL: SOS Rituals Glow Away Blemish Spot Treatment
NDC: 85179-007 | Form: LOTION
Manufacturer: I World LLC
Category: otc | Type: HUMAN OTC DRUG LABEL
Date: 20250314

ACTIVE INGREDIENTS: SALICYLIC ACID 5 mg/1 g
INACTIVE INGREDIENTS: WATER; PROPANEDIOL; GLYCERYL MONOSTEARATE; CETOSTEARYL ALCOHOL; ETHYLHEXYL STEARATE; TITANIUM DIOXIDE; PALMITIC ACID; STEARIC ACID; BETAINE; CETEARETH-25; CETEARETH-6; 1,2-HEXANEDIOL; HYDROXYACETOPHENONE; MAGNESIUM ALUMINUM SILICATE; AMMONIUM ACRYLOYLDIMETHYLTAURATE, DIMETHYLACRYLAMIDE, LAURYL METHACRYLATE AND LAURETH-4 METHACRYLATE COPOLYMER, TRIMETHYLOLPROPANE TRIACRYLATE CROSSLINKED (45000 MPA.S); SALIX ALBA BARK; SODIUM HYDROXIDE; POTASSIUM HYDROXIDE; ALUMINUM HYDROXIDE; POTASSIUM AZELOYL DIGLYCINATE; ALOE VERA LEAF; ZINC OXIDE; ASCORBYL GLUCOSIDE; TEA TREE OIL; OPUNTIA FICUS-INDICA WHOLE; FERRIC OXIDE RED; LINALOOL, (+/-)-; LIMONENE, (+)-; TURPENTINE; CAMPHOR (SYNTHETIC); HEXAMETHYLINDANOPYRAN; LINALYL ACETATE; TERPINEOL; EUCALYPTUS OIL; PINENE

SOS Rituals Glow Away Blemish Spot Treatment

Active ingredients

Salicylic Acid 0.5%

Purpose

Acne Treatment

Uses

For treatment of acne.

Warnings

For external use only.

Do not use

- on damaged or broken skin.

When using this product

- Keep out of eyes. Rinse with water to remove.

Stop use and ask doctor if

- rash occurs.

Keep out of reach of children.

- If product is swallowed get medical help or contact a poison control center right away.

Directions

Apply directly onto blemishes and leave on overnight. Massage a thin layer into the blemish and then add a thicker layer on top. Wash off in the morning.

Other information

Protect the product in this container from excessive heat and direct sun.

Inactive ingredients

WATER (AQUA), CANADIAN COLLOIDAL CLAY, VOLCANIC SOIL, PROPANEDIOL, GLYCERYL STEARATE, CETEARYL ALCOHOL, ETHYLHEXYL STEARATE, TITANIUM DIOXIDE, PALMITIC ACID, STEARIC ACID, BETAINE, CETEARETH-25, CETEARETH-6, 1, 2-HEXANEDIOL, HYDROXYACETOPHENONE, MAGNESIUM ALUMINUM SILICATE, POLYACRYLATE CROSSPOLYMER-6, SALIX ALBA (WILLOW) BARK EXTRACT, SODIUM HYDROXIDE. FRAGRANCE (PARFUM), POTASSIUM HYDROXIDE, ALUMINUM HYDROXIDE, POTASSIUM AZELOYL DIGLYCINATE, ALOE BARBADENSIS LEAF JUICE, LACTOBACILLUS FERMENT, ZINC OXIDE, ASCORBYL GLUCOSIDE, MELALEUCA ALTERNIFOLIA (TEA TREE) LEAF OIL , OPUNTIA FICUS-INDICA EXTRACT, IRON OXIDES, LINALOOL, LIMONENE, TURPENTINE, CAMPHOR, HEXAMETHYLINDANOPYRAN, LINALYL ACETATE, TERPINEOL, EUCALYPTUS GLOBULUS LEAF OIL, EUCALYPTUS GLOBULUS LEAF/TWiG OIL, PINENE.

Questions or comments?

1-212-244-5170